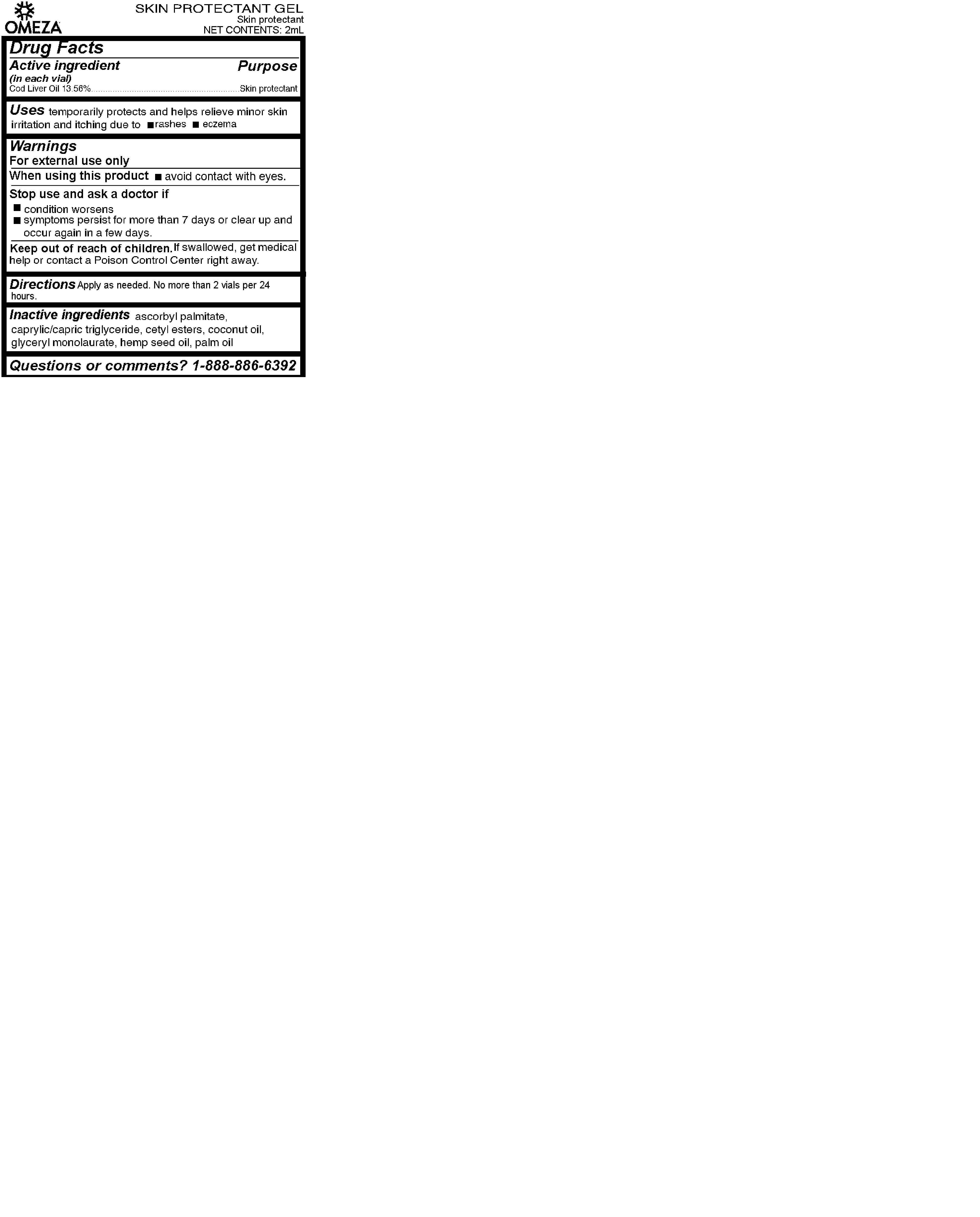 DRUG LABEL: Omeza Skin Protectant Gel
NDC: 73033-007 | Form: GEL
Manufacturer: Omeza LLC
Category: otc | Type: HUMAN OTC DRUG LABEL
Date: 20230116

ACTIVE INGREDIENTS: COD LIVER OIL 14.24 g/100 mL
INACTIVE INGREDIENTS: MEDIUM-CHAIN TRIGLYCERIDES; COCONUT OIL; ASCORBYL PALMITATE; CETYL ESTERS WAX; GLYCERYL LAURATE; CANNABIS SATIVA SEED OIL; PALM OIL

Omeza Skin Protectant Gel 06 January 2023

Uses

Uses temporarily protects and helps relieve minor skin irritation and itching due to

- rashes
- eczema

Warnings

For external use only

When using this product

- avoid contact with eyes.

Stop use and ask a doctor if

- condition worsens
- symptoms persist for more than 7 days or clear up and occur again in a few days.

Keep out of reach of children. If swallowed, get medical help or contact a Poison Control Center right away.

Directions

Directions Apply as needed. No more than 2 vials per 24 hours.

Inactive Ingredients

ascorbyl palmitate, caprylic/capric triglyceride, cetyl esters, coconut oil, glyceryl monolaurate, hemp seed oil, palm oil

Questions or Comments? 1-888-886-6392

Drug Facts

Active ingredient

(in each vial)

Cod Liver Oil 13.56%

Purpose

Skin Protectant